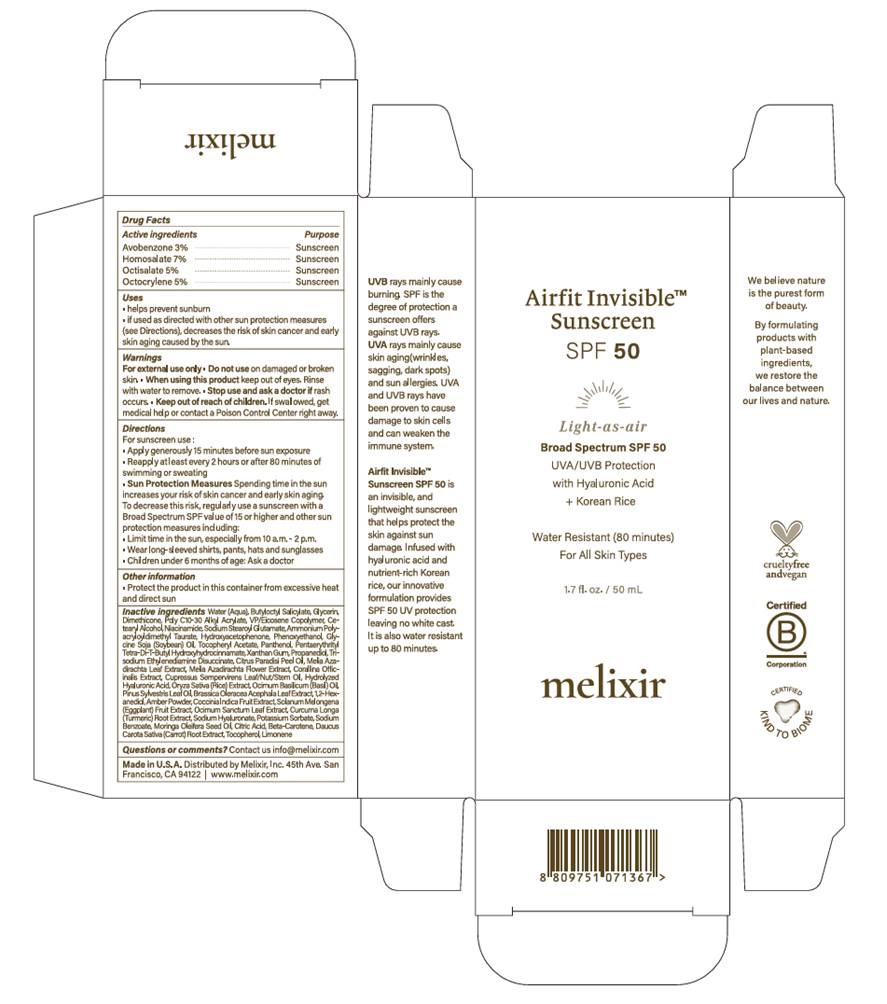 DRUG LABEL: Airfit Invisible Sunscreen
NDC: 87038-100 | Form: CREAM
Manufacturer: Melixir Inc.
Category: otc | Type: HUMAN OTC DRUG LABEL
Date: 20250824

ACTIVE INGREDIENTS: AVOBENZONE 30 mg/1 mL; HOMOSALATE 70 mg/1 mL; OCTISALATE 50 mg/1 mL; OCTOCRYLENE 50 mg/1 mL
INACTIVE INGREDIENTS: XANTHAN GUM; AZADIRACHTA INDICA FLOWER; CORALLINA OFFICINALIS; PENTAERYTHRITYL TETRA-DI-T-BUTYL HYDROXYHYDROCINNAMATE; TRISODIUM ETHYLENEDIAMINE DISUCCINATE; 1,2-HEXANEDIOL; COCCINIA GRANDIS FRUIT; HYALURONIC ACID; MORINGA OLEIFERA SEED OIL; OCIMUM BASILICUM (BASIL) OIL; BEHENYL ACRYLATE POLYMER; CETEARYL ALCOHOL; SODIUM HYALURONATE; AMBER POWDER; SODIUM BENZOATE; BUTYLOCTYL SALICYLATE; CUPRESSUS SEMPERVIRENS OIL; KALE; NIACINAMIDE; GRAPEFRUIT OIL; WATER; GLYCERIN; SODIUM STEAROYL GLUTAMATE; AMMONIUM POLYACRYLOYLDIMETHYL TAURATE; PANTHENOL; RICE GERM; HOLY BASIL LEAF; CURCUMA LONGA (TURMERIC) ROOT; CARROT; HYDROXYACETOPHENONE; POTASSIUM SORBATE; GLYCINE SOJA (SOYBEAN) OIL UNSAPONIFIABLES; CITRIC ACID; BETA-CAROTENE; TOCOPHEROL; VINYLPYRROLIDONE/EICOSENE COPOLYMER; .ALPHA.-TOCOPHEROL ACETATE, D-; PROPANEDIOL; MELIA AZADIRACHTA LEAF; DIMETHICONE; PINUS SYLVESTRIS LEAF OIL; PHENOXYETHANOL; EGGPLANT; LIMONENE, (+)-

Active ingredients

Avobenzone 3%
Homosalate 7%
Octisalate 5%
Octocrylene 5%

USES

· helps prevent sunburn
. if used as directed with other sun protection measures
(see Directions), decreases the risk of skin cancer and early
skin aging caused by the sun.

Warnings

- For external use only
- Do not use on damaged or broken skin.
- When using this product keep out of eyes
- Rinse with water to remove.
- Stop use and ask a doctor if rash occurs.
- Keep out of reach of children. If swallowed, get medical help or contact a Poison Control Center right away.

Directions

- For sunscreen use:

-Apply generously 15 minutes before sun exposure.

-Reapply at least every 2 hours or after 80 minutes of swimming or sweating.

- Sun Protection Measures

Spending time in the sun increases your risk of skin cancer and early skin aging.
To decrease this risk, regularly use a sunscreen with a Broad Spectrum SPF value of 15 or higher and other sun protection measures including:

-Limit time in the sun, especially from 10 a.m. - 2 p.m.

-Wear long-sleeved shirts, pants, hats and sunglasses.

- Children under 6 months of age:

-Ask a doctor.

Inactive ingredients

Water (Aqua), Butyloctyl Salicylate, Glycerin,
Dimethicone, Poly C10-30 Alkyl Acrylate, VP/Eicosene Copolymer, Ce-
tearyl Alcohol Niacinamide, Sodium Stearoyl Glutamate, Ammonium Poly-
acryloyldimethyl Taurate, Hydroxyacetophenone, Phenoxyethanol, Gly-
cine Soja (Soybean) Ol, Tocopheryl Acetate, Panthenol, Pentaerythrityl
Tetra-Di-T-Butyl Hydroxyhydrocinnamate, Xanthan Gum, Propanediol, Tri-
sodium Ethylenediamine Disuccinate, Citrus Paradisi Peel Ol, Melia Aza-
dirachta Leaf Extract, Melia Azadirachta Flower Extract, Corallina Offic
inalis Extract, Cupressus Sempervirens Leaf/Nut/Stem Oil, Hydrolyzed
Hyaluronic Acid, Oryza Sativa (Rice) Extract, Ocimum Basilicum (Basil) ol,
Pinus Sylvestris Leaf Oil, Brassica Oleracea Acephala Leaf Extract, 1,2-Hex-
anediol, Amber Powder, Coccinia Indica Fruit Extract, Solanum Melongena
(Eggplant) Fruit Extract, Ocimum Sanctum Leaf Extract, Curcuma Longa
(Turmeric) Root Extract, Sodium Hyaluronate, Potassium Sorbate, Sodium
Benzoate, Moringa Oleifera Seed Oil, Citric Acid, Beta-Carotene, Daucus
Carota Sativa (Carrot) Root Extract, Tocopherol, Limonene

Indication & Usage

- helps prevent sunbumn
- if used as directed with other sun protection measures (see Directions), decreases the risk of skin cancer and early skin aging caused by the sun.

Keep out of reach of childern

- Keep out of reach of children. If swallowed, get medical help or contact a Poison Control Center right away.

Purpose

- helps prevent sunbumn
- if used as directed with other sun protection measures (see Directions), decreases the risk of skin cancer and early

skin aging caused by the sun.

PACKAGE LABEL

Airfit Invisible™
Sunscreen
SPF 50

Broad Spectrum

1.7 fl. oz. / 50 mL

melixir